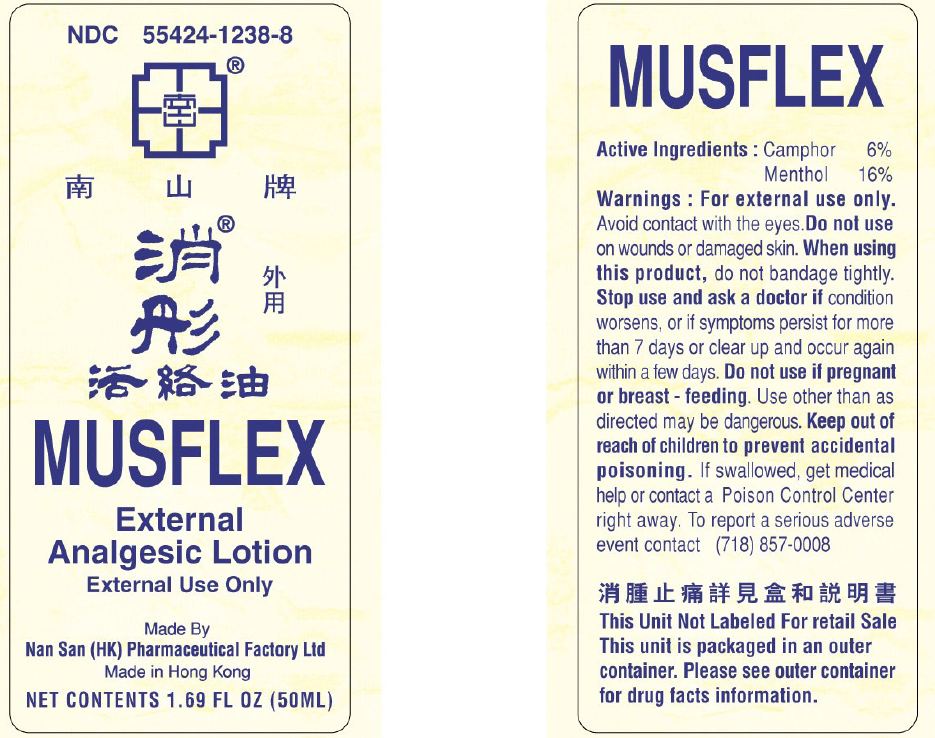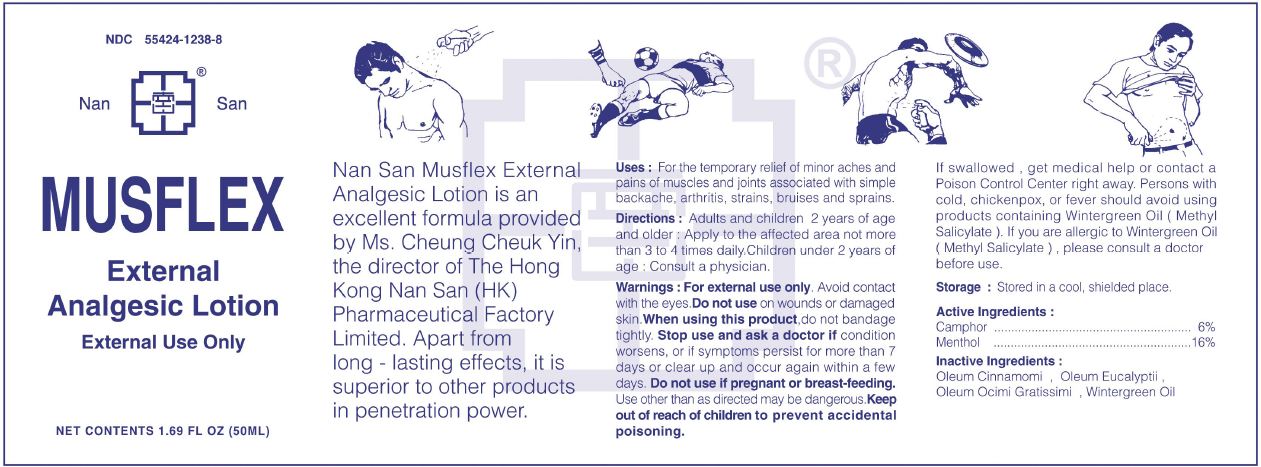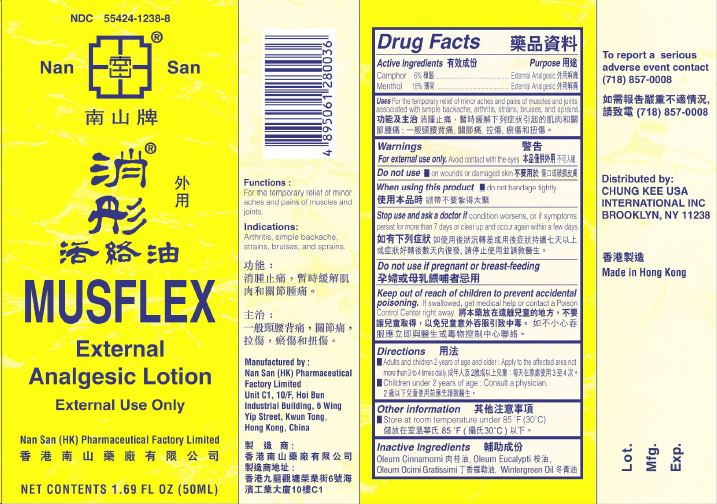 DRUG LABEL: Nan San MUSFLEX External Analgesic
NDC: 55424-1238 | Form: LOTION
Manufacturer: CHUNG KEE USA INTERNATIONAL INC
Category: otc | Type: HUMAN OTC DRUG LABEL
Date: 20180306

ACTIVE INGREDIENTS: CAMPHOR (NATURAL) 60 mg/1 mL; MENTHOL 160 mg/1 mL
INACTIVE INGREDIENTS: CINNAMON OIL; EUCALYPTUS OIL; OCIMUM GRATISSIMUM LEAF OIL; METHYL SALICYLATE

Nan San MUSFLEX External Analgesic Lotion

Active Ingredients

Camphor 6%

Menthol 16%

Purpose

External Analgesic

Uses

For the temporary relief of minor aches and pains of muscles and joints associated with simple backache, arthritis, strains, bruises, and sprains.

Warnings

For external use only.

Avoid contact with the eyes.

Do not use

- on wounds or damaged skin

When using this product

- do not bandage tightly

Stop use and ask a doctor if

condition worsens, or if symptoms persist for more than 7 days or clear up and occur again within a few days.

If pregnant or breast-feeding

ask a health professional before use.

Keep out of reach of children to prevent accidental poisoning.

if swallowed, get medical help or contact a Poison Control Center right away.

Directions

- Adults and children 2 years of age and older: Apply to the affected area not more than 3 to 4 times daily
- Children under 2 years of age: Consult a physician

Other Information

- Store at room temperature under 85 degrees F (30 degrees C)

Inactive Ingredients

Oleum Cinnamoni, Oleum Eucalypti, Oleum Ocimi Gratissimi, Wintergreen Oil

Manufactured By:

Nan San (HK) Pharmaceutical Factory Limited

Unit C1, 10/f, Hoi Bun

Industrial Building, 6 Wing Yip Street,

Kwun Tong, Hong Kong, China.